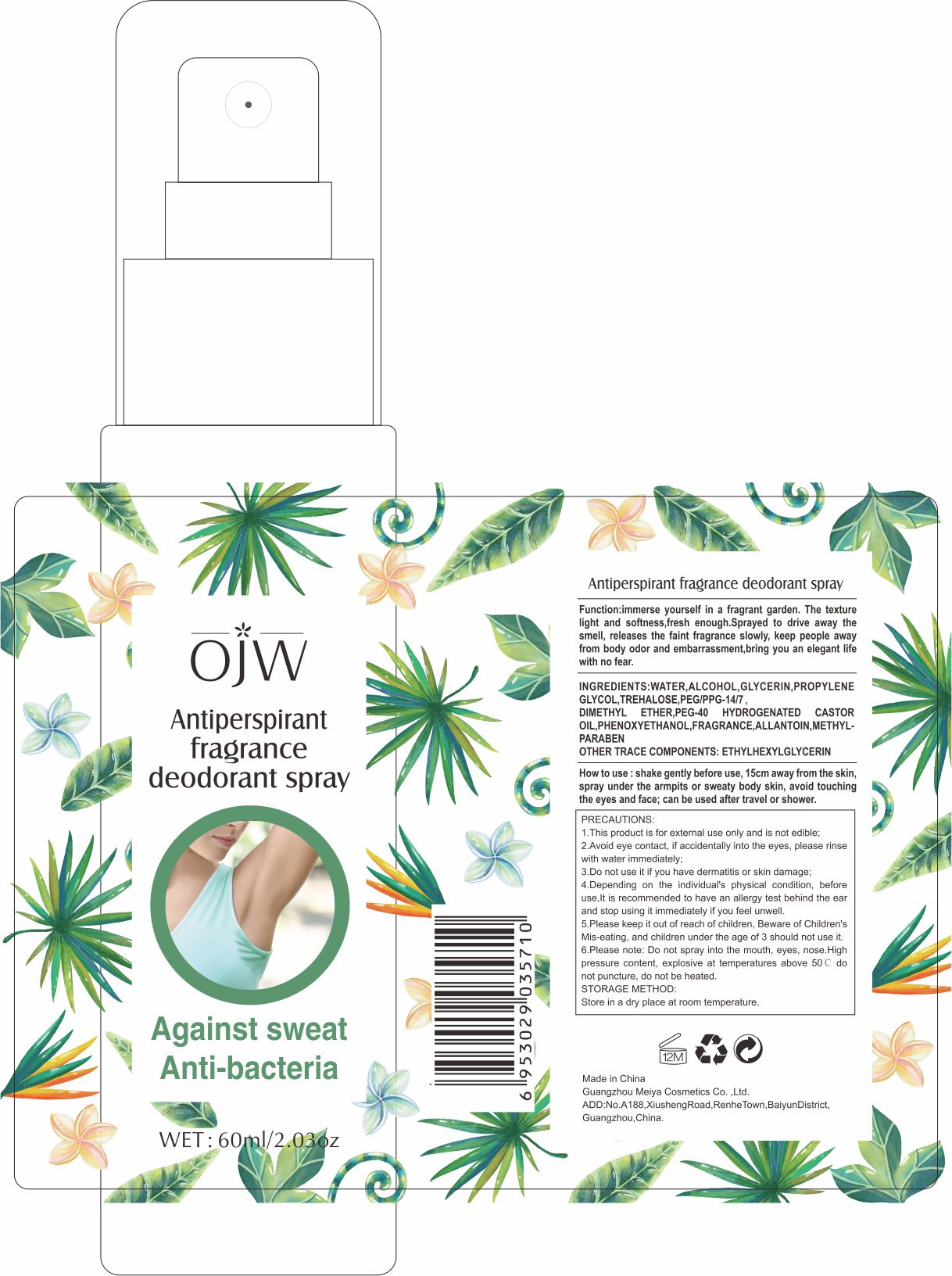 DRUG LABEL: Antiperspirant
NDC: 84673-007 | Form: EMULSION
Manufacturer: Guangzhou Meiya Cosmetics Co., Ltd.
Category: otc | Type: HUMAN OTC DRUG LABEL
Date: 20240917

ACTIVE INGREDIENTS: ALUMINUM CHLOROHYDRATE 4.4 g/1 mg
INACTIVE INGREDIENTS: ETHYLHEXYLGLYCERIN 0.5 g/1 mg; WATER 30 g/1 mg; PEG/PPG-14/7 DIMETHYL ETHER 1 g/1 mg; ALCOHOL 5 g/1 mg; ALLANTOIN 2 g/1 mg; TREHALOSE 2 g/1 mg; PHENOXYETHANOL 0.5 g/1 mg; METHYLPARABEN 1.5 g/1 mg; GLYCERIN 3 g/1 mg

ACTIVE INGREDIENT

ALUMINUM CHLOROHYDRATE 4.4%

PURPOSE

Function:Immerse yourself in a fragrant garden. the texture light and softness,fresh enough.Sprayed to drive away the smell, releases the faint fragrance slowly, keep people away from body odor and embarrassment,bring you an elegant life with no fear.

INDICATIONS AND USAGE

HOW TO USE : Shake gently before use, 15cm away from the skin, spray under the armpits or sweaty body skin, avoid touching the eyes and face; can be used after travel or shower.

WARNINGS

Precautions:

1. This product is for external use only and is not edible;

2. Avoid eye contact, if accidentally into the eyes, please rinse with water immediately;

3. Do not use it if you have dermatitis or skin damage;

4. Depending on the individual's physical condition, before use,It is recommended to have an allergy test behind the ear and stop using it immediately if you feel unwell.

5. Please keep it out of reach of children, Beware of Children's Mis-eating, and children under the age of 3 should not use it.

6.Please note: Do not spray into the mouth, eyes, nose.High pressure content, explosive at temperatures above 50℃ do not puncture, do not be heated.

STOP USE

1. Avoid eye contact, if accidentally into the eyes, please rinse with water immediately;

2. Do not use it if you have dermatitis or skin damage;

3. Depending on the individual's physical condition, before use,It is recommended to have an allergy test behind the ear and stop using it immediately if you feel unwell.

DO NOT USE

1. This product is for external use only and is not edible;

2. Avoid eye contact, if accidentally into the eyes, please rinse with water immediately;

3. Do not use it if you have dermatitis or skin damage;

4. Depending on the individual's physical condition, before use,It is recommended to have an allergy test behind the ear and stop using it immediately if you feel unwell.

5. Please keep it out of reach of children, Beware of Children's Mis-eating, and children under the age of 3 should not use it.

6.Please note: Do not spray into the mouth, eyes, nose.High pressure content, explosive at temperatures above 50℃ do not puncture, do not be heated.

KEEP OUT OF REACH OF CHILDREN

Please keep it out of reach of children, Beware of Children's Mis-eating, and children under the age of 3 should not use it.

WHEN USING

1. This product is for external use only and is not edible;

2. Avoid eye contact, if accidentally into the eyes, please rinse with water immediately;

3. Do not use it if you have dermatitis or skin damage;

4. Depending on the individual's physical condition, before use,It is recommended to have an allergy test behind the ear and stop using it immediately if you feel unwell.

5. Please keep it out of reach of children, Beware of Children's Mis-eating, and children under the age of 3 should not use it.

6.Please note: Do not spray into the mouth, eyes, nose.High pressure content, explosive at temperatures above 50℃ do not puncture, do not be heated.

DOSAGE AND ADMINISTRATION

Shake gently before use, 15cm away from the skin, spray under the armpits or sweaty body skin, avoid touching the eyes and face; can be used after travel or shower.